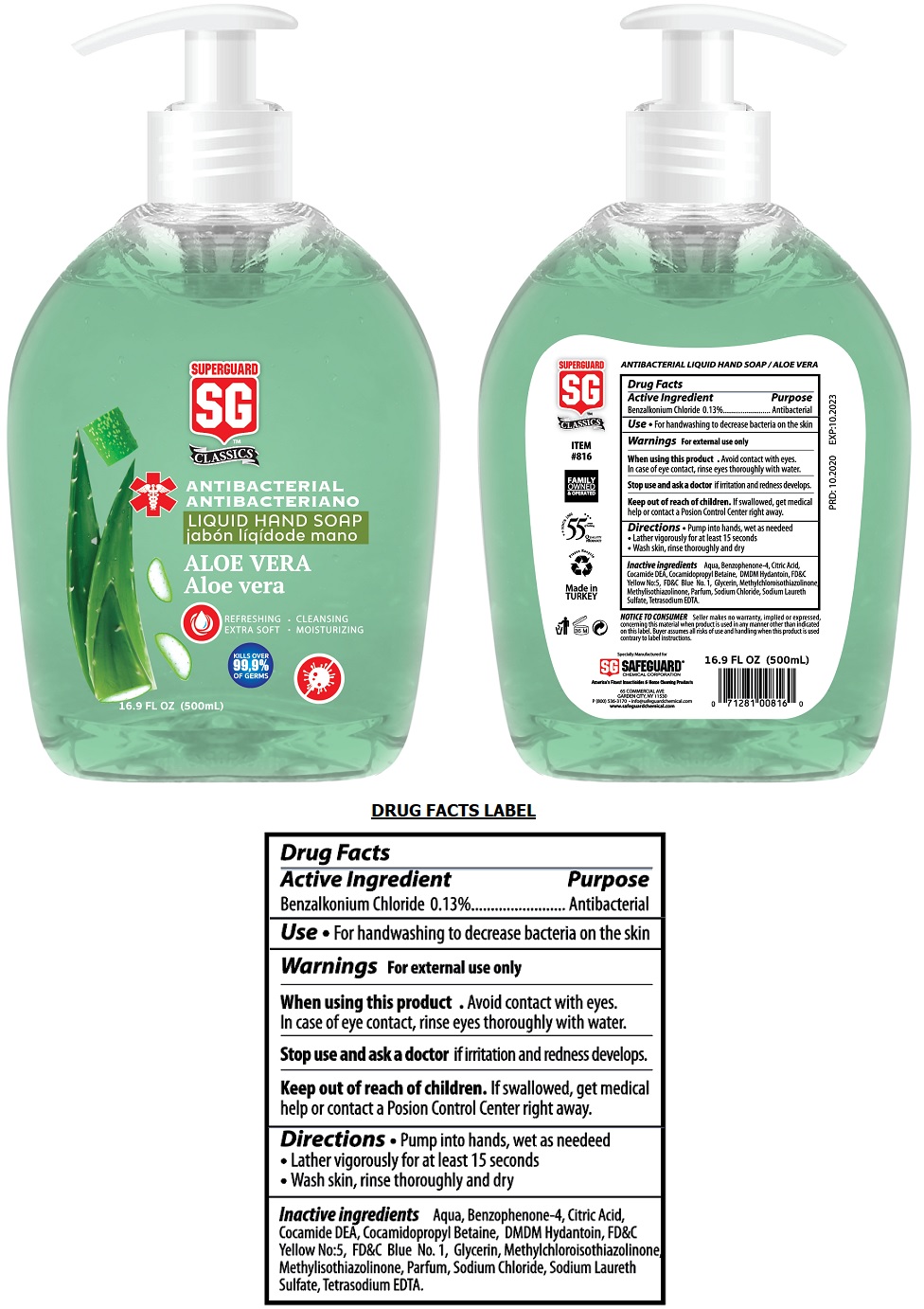 DRUG LABEL: SUPERGUARD Antibacterial Liquid HandSoap Aloe Vera
NDC: 40099-025 | Form: LIQUID
Manufacturer: Safeguard Chemical Corporation
Category: otc | Type: HUMAN OTC DRUG LABEL
Date: 20201221

ACTIVE INGREDIENTS: BENZALKONIUM CHLORIDE 0.13 g/100 mL
INACTIVE INGREDIENTS: WATER; SULISOBENZONE; CITRIC ACID MONOHYDRATE; COCO DIETHANOLAMIDE; COCAMIDOPROPYL BETAINE; DMDM HYDANTOIN; FD&C YELLOW NO. 5; FD&C BLUE NO. 1; GLYCERIN; METHYLCHLOROISOTHIAZOLINONE; METHYLISOTHIAZOLINONE; SODIUM CHLORIDE; SODIUM LAURETH-3 SULFATE; EDETATE SODIUM

SUPERGUARD ANTIBACTERIAL LIQUID HAND SOAP ALOE VERA

Active Ingredient

Benzalkonium Chloride 0.13%

Purpose

Antibacterial

Use

• For handwashing to decrease bacteria on the skin

Warnings

For external use only

When using this product • Avoid contact with eyes. In case of eye contact, rinse eyes thoroughly with water.

Stop use and ask a doctor if irritation and redness develops.

Keep out of reach of children. If swallowed, get medical help or contact a Poison Control Center right away.

Directions

• Pump into hands, wet as needed

• Lather vigorously for at least 15 seconds

• Wash skin, rinse thoroughly and dry

Inactive ingredients

Aqua, Benzophenone-4, Citric Acid, Cocamide DEA, Cocamidopropyl Betaine, DMDM Hydantoin, FD&C Yellow No:5, FD&C Blue No.1, Glycerin, Methylchloroisothiazolinone, Methylisothiazolinone, Parfum, Sodium Chloride, Sodium Laureth Sulfate, Tetrasodium EDTA.

SUPERGUARD SG™ CLASSICS

REFRESHING • CLEANSING

EXTRA SOFT • MOISTURIZING

KILLS OVER 99.9% OF GERMS

FAMILY OWNED & OPERATED

SINCE 1966

QUALITY PRODUCT

Made in TURKEY

NOTICE TO CONSUMER Seller makes no warranty, implied or expressed, concerning this material when product is used in any manner other than indicated on this label. Buyer assumes all risks of use and handling when this product is used contrary to label instructions.

Specially Manufactured for SAFEGUARD® CHEMICAL CORPORATION

America's Finest Insecticides & Home Cleaning Products

65 COMMERCIAL AVE

GARDEN CITY, NY 11530

P (800) 536-3170 • info@safeguardchemical.com

www.safeguardchemical.com